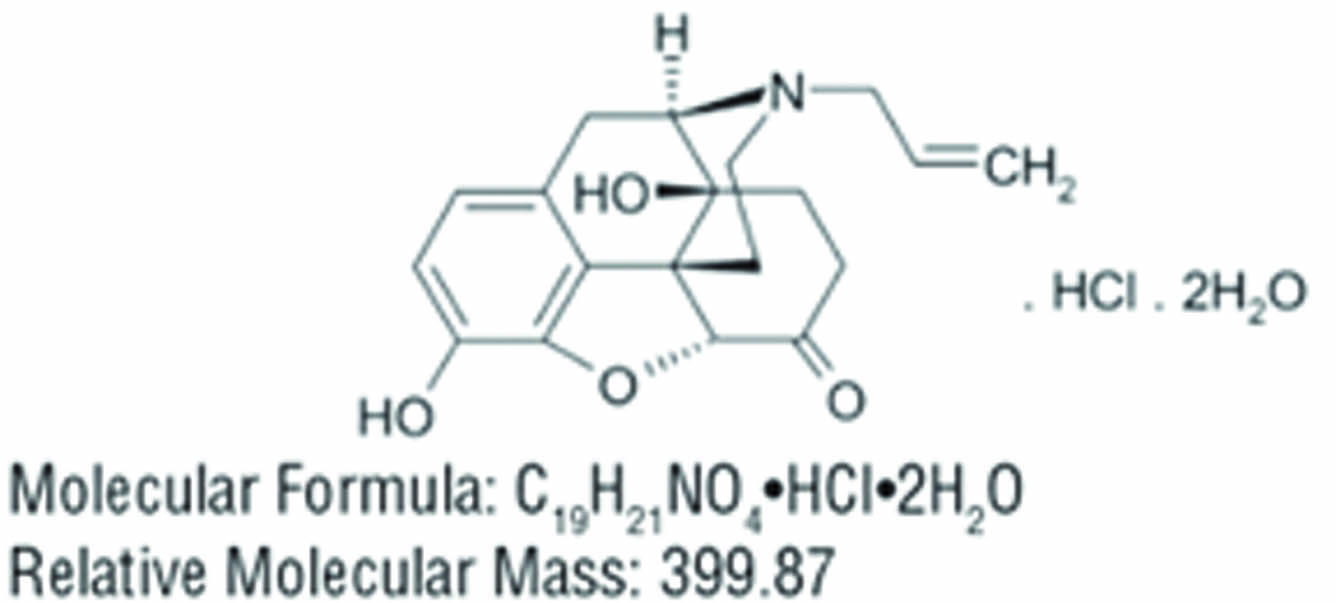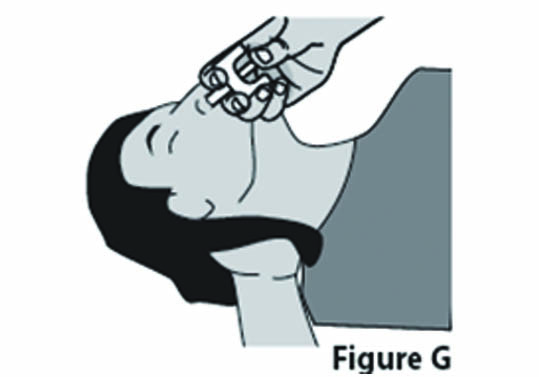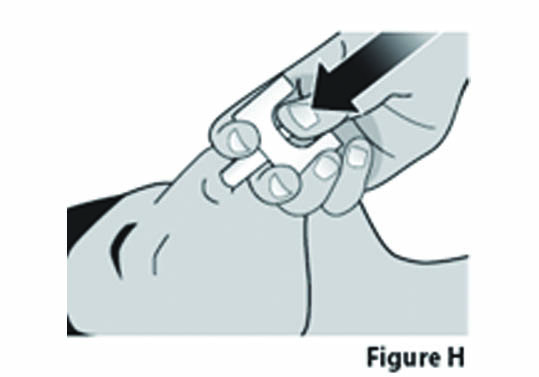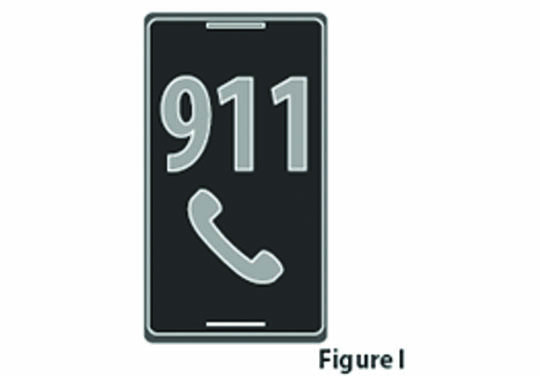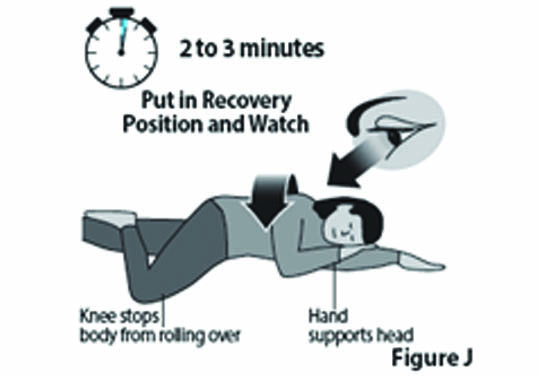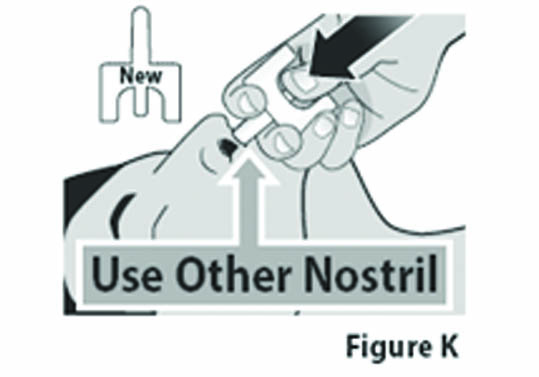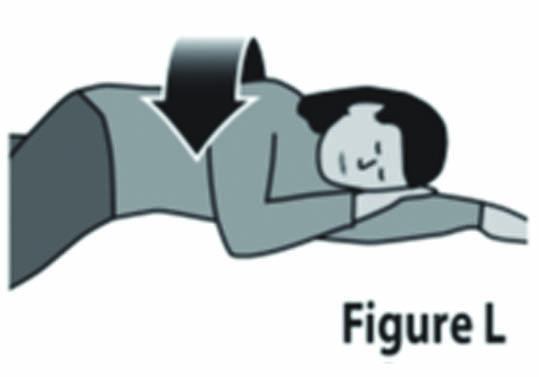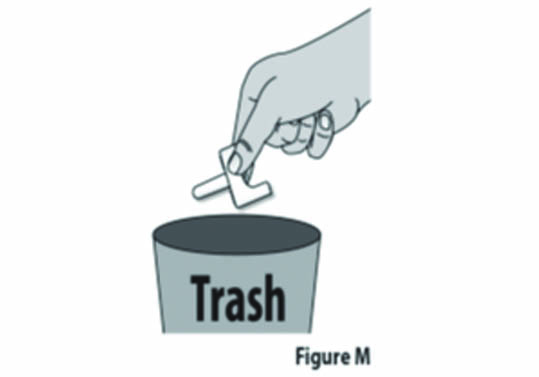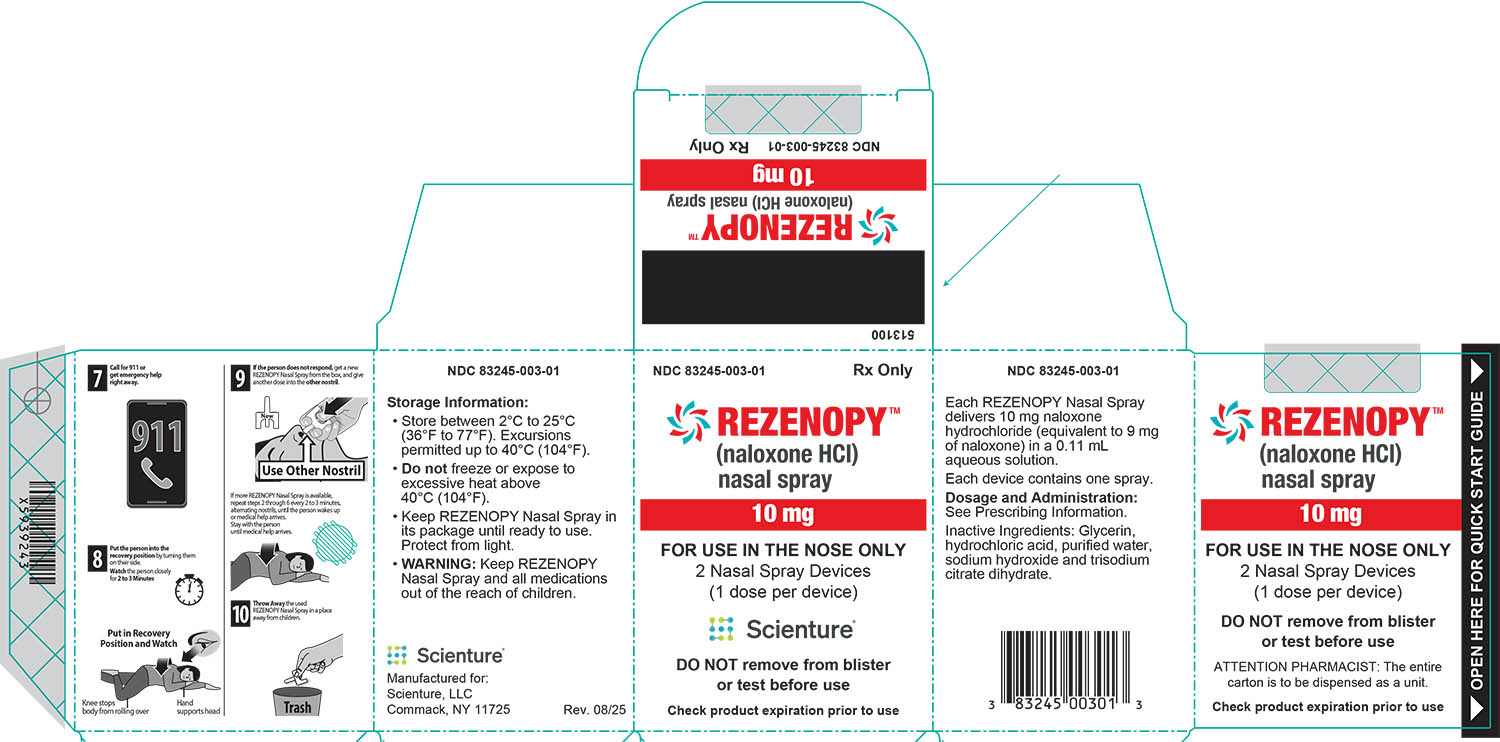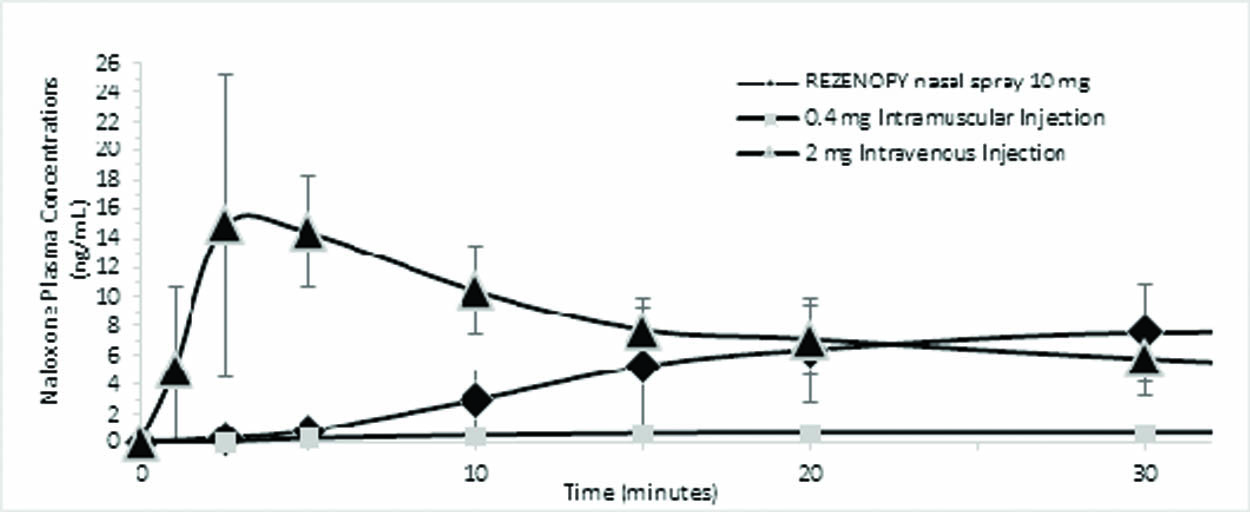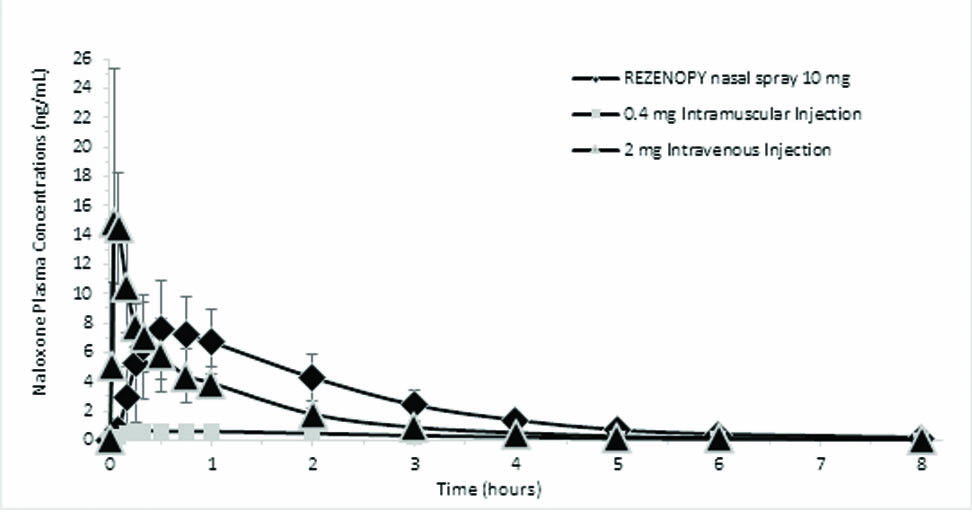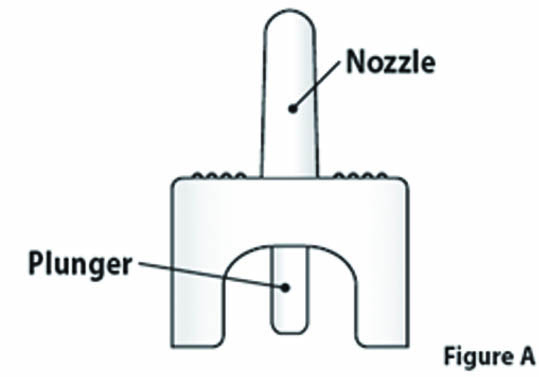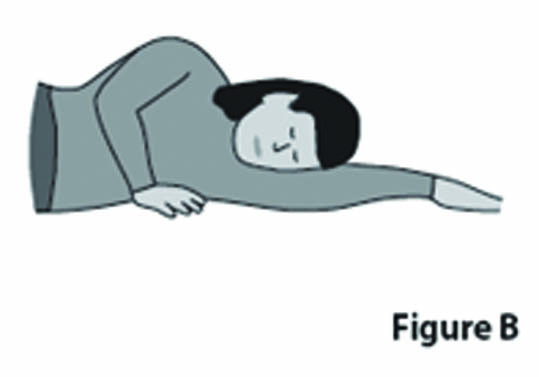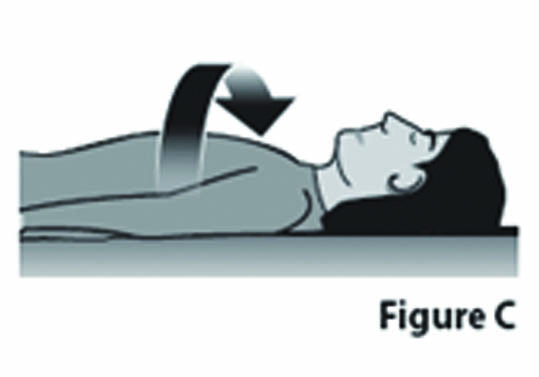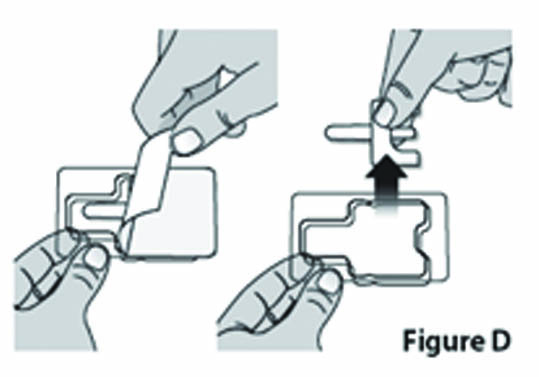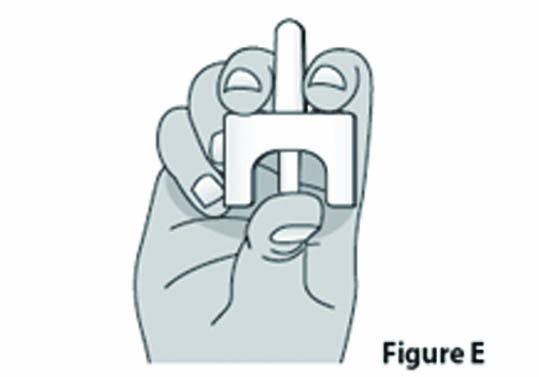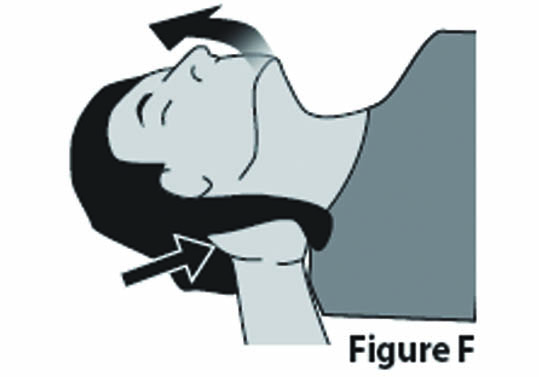 DRUG LABEL: REZENOPY
NDC: 83245-003 | Form: SPRAY
Manufacturer: Scienture LLC
Category: prescription | Type: HUMAN PRESCRIPTION DRUG LABEL
Date: 20260213

ACTIVE INGREDIENTS: NALOXONE HYDROCHLORIDE 10 mg/0.11 mL
INACTIVE INGREDIENTS: GLYCERIN; TRISODIUM CITRATE DIHYDRATE; HYDROCHLORIC ACID; SODIUM HYDROXIDE; WATER

HIGHLIGHTS OF PRESCRIBING INFORMATION

These highlights do not include all the information needed to use REZENOPY nasal spray safely and effectively.
See full prescribing information for REZENOPY nasal spray.
REZENOPY™ (naloxone HCl) nasal spray, 10 mg
Initial U.S. Approval:1971

1 INDICATIONS AND USAGE

REZENOPY nasal spray is an opioid antagonist for the emergency treatment of known or suspected opioid overdose, as manifested by respiratory and/or central nervous system depression in adult and pediatric patients. (1)

REZENOPY nasal spray is intended for immediate administration as emergency therapy in settings where opioids may be present. (1)

REZENOPY nasal spray is not a substitute for emergency medical care. (1)

2 DOSAGE AND ADMINISTRATION

- REZENOPY nasal spray is for intranasal use only. (2.1)
- Seek emergency medical care immediately after use. (2.1)
- Administration of a single spray of REZENOPY nasal spray intranasally into one nostril in adult and pediatric patients. (2.2)
- If the patient does not respond within 2 to 3 minutes or responds and then relapses into respiratory depression, an additional dose of REZENOPY nasal spray may be given into the other nostril with a new device. (2.2)
- Do not administer more than 2 sprays of REZENOPY nasal spray per day. (2.2)
- Additional supportive and/or resuscitative measures may be helpful while awaiting emergency medical assistance. (2.2)

3 DOSAGE FORMS AND STRENGTHS

Nasal spray: 10 mg of naloxone hydrochloride in 0.11 mL. (3)

4 CONTRAINDICATIONS

Hypersensitivity to naloxone hydrochloride. (4)

5 WARNINGS AND PRECAUTIONS

- Risk of Recurrent Respiratory and CNS Depression: Due to the duration of action of naloxone relative to the opioid, keep patient under continued surveillance and administer additional doses of REZENOPY nasal spray, as necessary, using a new nasal spray device while awaiting emergency medical assistance. (5.1)
- Risk of Limited Efficacy with Partial Agonists or Mixed Agonists/Antagonists: Reversal of respiratory depression caused by partial agonists or mixed agonists/antagonists, such as buprenorphine and pentazocine, may be incomplete. Larger or repeat doses may be required. (5.2)
- Precipitation of Severe Opioid Withdrawal: Use in patients who are opioid dependent may precipitate opioid withdrawal. In neonates, opioid withdrawal may be life- threatening if not recognized and properly treated. Monitor for the development of opioid withdrawal. (5.3)
- Risk of Cardiovascular (CV) Effects: Abrupt postoperative reversal of opioid depression may result in adverse CV effects. These events have primarily occurred in patients who had pre-existing CV disorders or received other drugs that may have similar adverse CV effects. Monitor these patients closely in an appropriate healthcare setting after use of naloxone hydrochloride. (5.3)

6 ADVERSE REACTIONS

The following adverse reactions were observed in a REZENOPY nasal spray clinical study: abdominal pain upper, nasopharyngitis, and dysgeusia. (6)

To report SUSPECTED ADVERSE REACTIONS, contact Scienture, LLC at 1-833-754-4917 or FDA at 1-800-FDA-1088 or www.fda.gov/medwatch

FULL PRESCRIBING INFORMATION

1 INDICATIONS AND USAGE

REZENOPY nasal spray is indicated for the emergency treatment of known or suspected opioid overdose, as manifested by respiratory and/or central nervous system depression in adult and pediatric patients.

REZENOPY nasal spray is intended for immediate administration as emergency therapy in settings where opioids may be present.

REZENOPY nasal spray is not a substitute for emergency medical care.

2 DOSAGE AND ADMINISTRATION

2.1 Important Administration Instructions

REZENOPY nasal spray is for intranasal use only.

All approved naloxone hydrochloride products achieve plasma concentrations that have been shown to be efficacious in reversing the effects of opioid overdose. Comparing different products on a nominal mg-for-mg basis may be misleading [see Clinical Pharmacology (12.3)].

Because treatment of suspected opioid overdose must be performed by someone other than the patient, instruct the prescription recipient to inform those around them about the presence of REZENOPY nasal spray and the Instructions for Use.

Instruct the patient or caregiver to read the Instructions for Use at the time they receive a prescription for REZENOPY nasal spray.

Emphasize the following instructions to the patient or caregiver:

- Seek medical care immediately after use. Since the duration of action of most opioids exceeds that of naloxone hydrochloride and the suspected opioid overdose may occur outside of supervised medical settings, seek immediate emergency medical assistance, keep the patient under continued surveillance until emergency personnel arrive, and administer additional doses of REZENOPY nasal spray, as necessary. Always seek emergency medical assistance in the event of a suspected, potentially life-threatening opioid emergency after administration of the first dose of REZENOPY nasal spray.
- Additional doses of REZENOPY nasal spray may be required before emergency medical assistance becomes available.
- Do not attempt to reuse REZENOPY nasal spray. Each REZENOPY nasal spray contains a single dose of naloxone.
- Re-administer REZENOPY nasal spray, using a new nasal spray, if the patient does not respond within 2 to 3 minutes or responds and then relapses into respiratory depression.
- Administer REZENOPY nasal spray in alternate nostrils with each dose.
- Administer REZENOPY nasal spray according to the printed instructions on the device label and the Instructions for Use.
- Place the patient in the supine position on their back. Prior to administration, be sure the device nozzle is inserted in either nostril of the patient, support the back of the neck and tilt the patient’s head back. Do not prime or test the device prior to administration.
- To administer the dose firmly press the bottom of the device plunger.
- Remove the device nozzle from the nostril after use.
- Turn patient on their side as shown in the Instructions for Use and call for emergency medical assistance immediately after administration of the first dose of REZENOPY nasal spray.

2.2 Dosing in Adult and Pediatric Patients

Initial Dosing

The recommended initial dose of REZENOPY nasal spray in adults and pediatric patients is one spray delivered by intranasal administration. Administer REZENOPY nasal spray as quickly as possible because prolonged respiratory depression may result in damage to the central nervous system or death.

Repeat Dosing

Seek emergency medical assistance as soon as possible after administering the first dose of REZENOPY nasal spray.

The requirement for repeat doses of REZENOPY nasal spray depends upon the amount, type, and route of administration of the opioid being antagonized.

Administer REZENOPY nasal spray in alternate nostrils with each dose.

If the desired response is not obtained after 2 to 3 minutes, administer a second dose of REZENOPY nasal spray using a new REZENOPY nasal spray device. If there is still no response and additional doses are available, administer additional doses of REZENOPY every 2 to 3 minutes, alternating nostrils and using a new REZENOPY, until emergency medical assistance arrives. Additional supportive and/or resuscitative measures may be helpful while awaiting emergency medical assistance.

If the patient responds to REZENOPY nasal spray and relapses back into respiratory depression before emergency assistance arrives, administer an additional dose of REZENOPY nasal spray using a new REZENOPY nasal spray device and continue surveillance of the patient.

2.3 Dosing Modifications due to Partial Agonists or Mixed Agonist/Antagonists

Reversal of respiratory depression by partial agonists or mixed agonist/antagonists, such as buprenorphine and pentazocine, may be incomplete and require higher doses of naloxone hydrochloride or repeat administration of REZENOPY nasal spray using a new nasal spray device [see Warnings and Precautions (5.2)].

3 DOSAGE FORMS AND STRENGTHS

Nasal Spray: 10 mg of naloxone hydrochloride in 0.11 mL in a single dose nasal spray.

4 CONTRAINDICATIONS

REZENOPY nasal spray is contraindicated in patients known to be hypersensitive to naloxone hydrochloride or to any of the other ingredients.

5 WARNINGS AND PRECAUTIONS

5.1 Risk of Recurrent Respiratory and Central Nervous System Depression

The duration of action of most opioids may exceed that of REZENOPY nasal spray resulting in a return of respiratory and/or central nervous system depression after an initial improvement in symptoms. Therefore, it is necessary to seek emergency medical assistance immediately after administration of the first dose of REZENOPY nasal spray and to keep the patient under continued surveillance. Administer additional doses of REZENOPY nasal spray if the patient does not adequately respond or responds and then relapses back into respiratory depression, as necessary [see Dosage and Administration (2.2)]. Additional supportive and/or resuscitative measures may be helpful while awaiting emergency medical assistance.

5.2 Risk of Limited Efficacy with Partial Agonists or Mixed Agonist/Antagonists

Reversal of respiratory depression by partial agonists or mixed agonist/antagonists such as buprenorphine and pentazocine, may be incomplete. Larger or repeat doses of naloxone hydrochloride may be required to antagonize buprenorphine because the latter has a long duration of action due to its slow rate of binding and subsequent slow dissociation from the opioid receptor [see Dosage and Administration (2.2)].

Buprenorphine antagonism is characterized by a gradual onset of the reversal effects and a decreased duration of action of the normally prolonged respiratory depression.

5.3 Precipitation of Severe Opioid Withdrawal

The use of REZENOPY nasal spray in patients who are opioid dependent may precipitate opioid withdrawal characterized by the following signs and symptoms: body aches, diarrhea, tachycardia, fever, runny nose, sneezing, piloerection, sweating, yawning, nausea or vomiting, nervousness, restlessness or irritability, shivering or trembling, abdominal cramps, weakness, and increased blood pressure. In neonates, opioid withdrawal may be life-threatening if not recognized and properly treated and may include the following signs and symptoms: convulsions, excessive crying, and hyperactive reflexes. Monitor the patient for the development of the signs and symptoms of opioid withdrawal.

Abrupt postoperative reversal of opioid depression after using naloxone hydrochloride may result in nausea, vomiting, sweating, tremulousness, tachycardia, hypotension, hypertension, seizures, ventricular tachycardia and fibrillation, pulmonary edema, and cardiac arrest. Death, coma, and encephalopathy have been reported as sequelae of these events. These events have primarily occurred in patients who had pre-existing cardiovascular disorders or received other drugs that may have similar adverse cardiovascular effects. Although a direct cause and effect relationship has not been established, after use of naloxone hydrochloride, monitor patients with pre-existing cardiac disease or patients who have received medications with potential adverse cardiovascular effects for hypotension, ventricular tachycardia or fibrillation, and pulmonary edema in an appropriate healthcare setting. It has been suggested that the pathogenesis of pulmonary edema associated with the use of naloxone hydrochloride is similar to neurogenic pulmonary edema, i.e., a centrally mediated massive catecholamine response leading to a dramatic shift of blood volume into the pulmonary vascular bed resulting in increased hydrostatic pressures.

There may be clinical settings, particularly the postpartum period in neonates with known or suspected exposure to maternal opioid use, where it is preferable to avoid the abrupt precipitation of opioid withdrawal symptoms. In these settings, consider use of an alternative, naloxone containing product that can be titrated to effect and, where applicable, dosed according to weight [see Use in Specific Population (8.4)].

6 ADVERSE REACTIONS

The following serious adverse reactions are discussed elsewhere in the labeling:

- Precipitation of Severe Opioid Withdrawal [see Warnings and Precautions (5.3)].

Because clinical studies are conducted under widely varying conditions, adverse reaction rates observed in the clinical studies of a drug cannot be directly compared to the rates in the clinical studies of another drug and may not reflect the rates observed in practice.

The following adverse reactions were observed in a REZENOPY nasal spray clinical study.

In a pharmacokinetic study of 30 healthy adult volunteers exposed to one spray of REZENOPY nasal spray, adverse reactions of abdominal pain upper, nasopharyngitis and dysgeusia were observed.

The following adverse reactions have been identified primarily during post-approval use of naloxone hydrochloride in the post-operative setting. Because these reactions are reported voluntarily from a population of uncertain size, it is not always possible to reliably estimate their frequency or establish a causal relationship to drug exposure: Hypotension, hypertension, ventricular tachycardia and fibrillation, dyspnea, pulmonary edema, and cardiac arrest. Death, coma, and encephalopathy have been reported as sequelae of these events. Excessive doses of naloxone hydrochloride in post-operative patients have resulted in significant reversal of analgesia, and have caused agitation.

Abrupt reversal of opioid effects in persons who were physically dependent on opioids has precipitated an acute withdrawal syndrome. Signs and symptoms have included: body aches, fever, sweating, runny nose, sneezing, piloerection, yawning, weakness, shivering or trembling, nervousness, restlessness or irritability, diarrhea, nausea or vomiting, abdominal cramps, increased blood pressure, tachycardia. In some patients, there may be aggressive behavior upon abrupt reversal of an opioid overdose. In the neonate, opioid withdrawal signs and symptoms also included convulsions, excessive crying, and hyperactive reflexes.

8 USE IN SPECIFIC POPULATIONS

8.1 Pregnancy

Risk Summary

Life-sustaining therapy for opioid overdose should not be withheld (see Clinical Considerations). Available data from retrospective cohort studies on naloxone use in pregnant women have not identified a drug-associated risk of major birth defects, miscarriage, or other adverse maternal or fetal outcomes. In animal reproduction studies, no embryotoxic or teratogenic effects were observed in mice and rats administered naloxone hydrochloride during organogenesis at doses equivalent to 2-times and 4-times, respectively, a human dose of 20 mg/day (2 sprays of Rezenopy) (see Data).

The background risk of major birth defects and miscarriage for the indicated population is unknown. All pregnancies have a background risk of birth defect, loss, or other adverse outcomes. In the U.S. general population, the estimated background risk of major birth defects and miscarriage in clinically recognized pregnancies is 2 to 4% and 15 to 20%, respectively.

Clinical Considerations

Disease-associated maternal and/or embryo/fetal risk

An opioid overdose is a medical emergency and can be fatal for the pregnant woman and fetus if left untreated. Treatment with Rezenopy for opioid overdose should not be withheld because of potential concerns regarding the effects of Rezenopy on the fetus.

Data

Animal Data

Naloxone hydrochloride was administered during organogenesis to mice and rats at doses 2-times and 4-times, respectively, a human dose of 20 mg (two REZENOPY nasal sprays) based on body surface area comparison. These studies demonstrated no embryotoxic or teratogenic effects due to naloxone hydrochloride.

8.2 Lactation

Risk Summary

There is no information available on the presence of naloxone in human or animal milk, the effects of the drug on the breastfed infant, or the effects of the drug on milk production.

Published studies in lactating women have shown that naloxone does not effect prolactin and oxytocin hormone levels. Naloxone is minimally orally bioavailable.

8.4 Pediatric Use

The safety and effectiveness of Rezenopy for known or suspected opioid overdose as manifested by respiratory and/or central nervous system depression have been established in pediatric patients Use of naloxone hydrochloride in pediatric patients is supported by adult bioequivalence studies coupled with evidence from the safe and effective use of other naloxone hydrochloride drug products. No pediatric studies were conducted for REZENOPY nasal spray.

Absorption of naloxone hydrochloride following intranasal administration in pediatric patients may be erratic or delayed. Even when the opiate-intoxicated pediatric patient responds appropriately to naloxone hydrochloride, he/she must be carefully monitored for at least 24 hours, as a relapse may occur as naloxone hydrochloride is metabolized.

In opioid-dependent pediatric patients, (including neonates), administration of naloxone hydrochloride may result in an abrupt and complete reversal of opioid effects, precipitating an acute opioid withdrawal syndrome. Neonatal opioid withdrawal syndrome, unlike opioid withdrawal syndrome in adults, may be life-threatening if not recognized, and should be treated according to protocols developed by neonatology experts [see Warnings and Precautions (5.3)].

In settings such as in neonates with known or suspected exposure to maternal opioid use, where it may be preferable to avoid the abrupt precipitation of opioid withdrawal symptoms, consider use of an alternate naloxone-containing product that can be dosed according to weight and titrated to effect.

Also, in situations where the primary concern is for infants at risk for opioid overdose, consider whether the availability of alternate naloxone-containing products may be better suited than REZENOPY nasal spray.

8.5 Geriatric Use

Geriatric patients have a greater frequency of decreased hepatic, renal, or cardiac function and of concomitant disease or other drug therapy. Therefore, the systemic exposure of naloxone hydrochloride can be higher in these patients.

Clinical studies of naloxone hydrochloride did not include sufficient numbers of subjects aged 65 and over to determine whether they respond differently from younger subjects. Other reported clinical experience has not identified differences in responses between the elderly and younger patients.

11 DESCRIPTION

Rezenopy (naloxone hydrochloride) nasal spray is a pre-filled, single dose intranasal spray. Chemically, naloxone hydrochloride is the hydrochloride salt of 17-Allyl-4,5α-epoxy- 3,14-dihydroxymorphinan-6-one hydrochloride with the following structure:

Naloxone hydrochloride, an opioid antagonist, occurs as a white, to slightly off-white powder or almost white crystalline powder and contains two molecules of water of hydration. It is freely soluble in water, in dilute acids, and in strong alkali; slightly soluble in ethanol. pKa values (proton on Nitrogen) are respectively 7.94 at 20°C and 7.82 at 37°C.

Each REZENOPY nasal spray delivers 10 mg naloxone hydrochloride (equivalent to 9 mg of naloxone) in a 0.11 mL aqueous solution.

Inactive ingredients include glycerin, trisodium citrate dihydrate, hydrochloric acid and sodium hydroxide to adjust pH, and purified water. The pH range is 3.9 to 4.5.

12 CLINICAL PHARMACOLOGY

12.1 Mechanism of Action

Naloxone hydrochloride is an opioid antagonist that antagonizes opioid effects by competing for the same receptor sites.

Naloxone hydrochloride reverses the effects of opioids, including respiratory depression, sedation, and hypotension. It can also reverse the psychotomimetic and dysphoric effects of agonist-antagonists such as pentazocine.

12.2 Pharmacodynamics

When naloxone hydrochloride is administered intravenously, the onset of action is generally apparent within two minutes. The time to onset of action is shorter for intravenous compared to subcutaneous or intramuscular routes of administration. The duration of action is dependent upon the dose and route of administration of naloxone hydrochloride.

12.3 Pharmacokinetics

In a pharmacokinetic study in 30 healthy adult subjects, the relative bioavailability (BA) of one nasal spray of a 10 mg total dose (0.11 mL of 91 mg/mL naloxone hydrochloride solution) was compared to a single dose of 0.4 mg naloxone hydrochloride intramuscular injection and a single dose of 2 mg of naloxone hydrochloride intravenous injection. For intranasal administration, the subjects were instructed not to breathe through the nose during administration of the nasal spray and remained fully supine for approximately one-hour post-dose. For intramuscular administration, naloxone was administered as a single injection in the gluteus maximus muscle. For intravenous administration, naloxone was administered as an intravenous bolus. The pharmacokinetic parameters obtained in the study are shown in Table 1.

Table 1 Mean Pharmacokinetic Parameters (CV%) for REZENOPY nasal spray, Intramuscular and Intravenous Injections of Naloxone HCl to Healthy Subjects

Parameter | Rezenopy Nasal Spray 10 mg (n=29) | Naloxone HCl 0.4 mg Intramuscular Injection (n=30) | Naloxone HCl 2 mg Intravenous Injection (n=23)
tmax(h)† | 0.75 (0.25, 1.03) | 0.50 (0.17, 2.00) | 0.08 (0.02, 0.18)
Cmax (ng/mL) | 9.11 (35.45) | 0.74 (36.63) | 18.41 (46.08)
AUCt; (h·ng/mL) | 19.19 (24.81) | 1.92 (19.75) | 12.18 (24.30)
AUC0-∞; (h·ng/mL) | 19.52 (24.78) | 1.98 (19.18) | 12.25 (24.22)
t&frac12; (h) | 1.33 (16.09) | 1.22 (18.48) | 1.18 (11.59)
Dose normalized absolute BA vs. IV†† | 0.34 (30.53) | 0.84 (29.06) | -

† tmax reported as median (minimum, maximum)

†† N=22 and N=23, respectively for REZENOPY nasal spray 10 mg and Naloxone HCl 0.4 mg Intramuscular Injection for Dose normalized absolute BA vs. IV

Figure 1 Mean ± SD Plasma Concentration of Naloxone 0-30 minutes Following Intranasal, Intramuscular and Intravenous Administration.

Figure 2 Mean ± SD Plasma Concentration of Naloxone 0-8 hours Following Intranasal, Intramuscular and Intravenous Administration.

Absorption

REZENOPY nasal spray showed median Tmax 0.75 hour. The median Tmax for the 0.4 mg naloxone hydrochloride intramuscular injection was 0.5 hour. The dose normalized absolute bioavailability of one dose (10 mg) of REZENOPY nasal spray and 0.4 mg of naloxone HCl intramuscular injection compared to 2 mg of naloxone HCl intravenous injection was 34% and 84% respectively.

Distribution

Following parenteral administration, naloxone is distributed in the body and readily crosses the placenta. Plasma protein binding occurs but is relatively weak. Plasma albumin is the major binding constituent, but significant binding of naloxone also occurs to plasma constituents other than albumin. It is not known whether naloxone is excreted into human milk.

Elimination

Following a single intranasal administration of REZENOPY nasal spray (10 mg dose of naloxone hydrochloride), the mean plasma half-life of naloxone in healthy adults was approximately 1.33 hours (16.09% CV) hours. Following the administrations of a 0.4 mg naloxone hydrochloride intramuscular injection and a 2 mg naloxone hydrochloride intravenous injection, the half-life was 1.22 hours (18.48% CV) and 1.18 hours (11.59% CV), respectively. In a neonatal study of naloxone hydrochloride injection, the mean (± SD) plasma half-life was observed to be 3.1 (± 0.5) hours.

Metabolism

Naloxone hydrochloride is metabolized in the liver, primarily by glucuronide conjugation, with naloxone-3-glucoronide as the major metabolite.

Excretion

After an oral or intravenous dose, about 25-40% of naloxone is excreted as metabolites in urine within 6 hours, about 50% in 24 hours, and 60-70% in 72 hours.

13 NONCLINICAL TOXICOLOGY

13.1 Carcinogenesis, Mutagenesis, Impairment of Fertility

Carcinogenesis

Long-term animal studies to evaluate the carcinogenic potential of naloxone have not been completed.

Mutagenesis

Naloxone was weakly positive in the Ames mutagenicity and in the in vitro human lymphocyte chromosome aberration test but was negative in the in vitro Chinese hamster V79 cell HGPRT mutagenicity assay and in the in vivo rat bone marrow chromosome aberration study.

Impairment of Fertility

Reproductive studies conducted in mice and rats at doses 2-times and 4-times, respectively, a human dose of 20 mg/day (from two nasal sprays of Rezenopy) based on body surface area comparison, demonstrated no adverse effects on fertility of naloxone hydrochloride.

16 HOW SUPPLIED

16.1 How Supplied

REZENOPY nasal spray 10 mg is supplied as a carton containing two (2) blister packages (NDC 83245-003-01) each with a single spray device.

REZENOPY nasal spray is not made with natural rubber latex.

16.2 Storage and Handling

Store REZENOPY nasal spray in the blister and cartons provided.

Store between 2°C to 25°C (36°F to 77°F). Excursions permitted up to 40°C (104°F). Do not freeze or expose to excessive heat above 40°C (104°F). Protect from light.

REZENOPY nasal spray may freeze at cold temperatures. If this happens, the device will not spray. If REZENOPY nasal spray is frozen and is needed in an emergency, do NOT wait for REZENOPY nasal spray to thaw. Get emergency medical help right away.

17 PATIENT COUNSELING INFORMATION

Advise the patient to read the FDA-approved patient labeling (Patient Information and Instructions for Use).

Recognition of Opioid Overdose

Instruct patients and their family members or caregivers about how to recognize the signs and symptoms of an opioid overdose such as the following:

- Extreme somnolence - inability to awaken a patient verbally or upon a firm sternal rub.
- Respiratory depression - this can range from slow or shallow respiration to no respiration in a patient who is unarousable.
- Other signs and symptoms that may accompany somnolence and respiratory depression include the following:
  - Miosis
  - Bradycardia and/or hypotension

Risk of Recurrent Respiratory and Central Nervous System Depression

Instruct patients and their family members or caregivers that, since the duration of action of most opioids may exceed that of REZENOPY nasal spray, they must seek immediate emergency medical assistance after the first dose of REZENOPY nasal spray and keep the patient under continued surveillance [see Dosage and Administration (2.2), Warnings and Precautions (5.2)].

Limited Efficacy for/with Partial Agonists or Mixed Agonist/Antagonists

Instruct patients and their family members or caregivers that the reversal of respiratory depression caused by partial agonists or mixed agonist/antagonists, such as buprenorphine and pentazocine, may be incomplete and may require higher doses of naloxone hydrochloride or repeat administration of REZENOPY nasal spray, using a new nasal spray [see Dosage and Administration (2.2), Warnings and Precautions (5.2)].

Precipitation of Severe Opioid Withdrawal

Instruct patients and their family members or caregivers that the use of REZENOPY nasal spray in patients who are opioid dependent may precipitate opioid withdrawal [see Warnings and Precautions (5.3), Adverse Reactions (6)].

Administration Instructions

Instruct patients and their family members or caregivers to:

- Ensure REZENOPY nasal spray is present whenever persons may be intentionally or accidentally exposed to an opioid overdose (i.e., opioid emergencies).
- Administer REZENOPY nasal spray as quickly as possible if a patient is unresponsive and an opioid overdose is suspected, even when in doubt, because prolonged respiratory depression may result in damage to the central nervous system or death. REZENOPY nasal spray is not a substitute for emergency medical care [see Dosage and Administration (2.1)].
- Lay the patient on their back, tilt the patient’s head back while supporting the neck and administer REZENOPY nasal spray into one nostril. [see Dosage and Administration (2.1)].
- Use each nasal spray only one time [see Dosage and Administration (2.1)].
- Turn patient on their side as shown in the Instructions for Use and call for emergency medical assistance immediately after administration of the first dose of REZENOPY nasal spray. Additional supportive and/or resuscitative measures may be helpful while awaiting emergency medical assistance [see Dosage and Administration (2.1)].
- Monitor the patient and administer an additional dose of REZENOPY nasal spray using a new REZENOPY nasal spray every 2 to 3 minutes, if the patient is not responding or responds and then relapses back into respiratory depression. Administer REZENOPY nasal spray in alternate nostrils with each dose [see Dosage and Administration (2.1)].
- Replace REZENOPY nasal spray before its expiration date.

Manufactured for: Scienture, LLC, Commack, NY 11725

513201

Rev. 02/2026

PATIENT INFORMATION

REZENOPY™ (reh zeh' noe pee)

(naloxone HCl)

nasal spray, 10 mg

You and your family members or caregivers should read this Patient Information leaflet before an opioid emergency happens. This information does not take the place of talking with your healthcare provider about your medical condition or your treatment.

What is the most important information I should know about REZENOPY nasal spray?

REZENOPY nasal spray is used to temporarily reverse the effects of opioid medicines. The medicine in REZENOPY nasal spray has no effect in people who are not taking opioid medicines. Always carry REZENOPY nasal spray with you in case of an opioid emergency.

1. Use REZENOPY nasal spray right away if you or your caregiver think signs or symptoms of an opioid emergency are present, even if you are not sure, because an opioid emergency can cause severe injury or death. Signs and symptoms of an opioid emergency may include:

- unusual sleepiness and you are not able to awaken the person with a loud voice or rubbing firmly on the middle of their chest (sternum)
- breathing problems including slow or shallow breathing in someone difficult to awaken or who looks like they are not breathing
- the black circle in the center of the colored part of the eye (pupil) is very small, sometimes called “pinpoint pupils”, in someone difficult to awaken

2. Family members, caregivers, or other people who may have to use REZENOPY nasal spray in an opioid emergency should know where REZENOPY nasal spray is stored and how to give it before an opioid emergency happens.

3. Call 911 or get emergency medical help right away after giving the first dose of REZENOPY nasal spray. Rescue breathing or CPR (cardiopulmonary resuscitation) may be given while waiting for emergency medical help.

4. The signs and symptoms of an opioid emergency can return after REZENOPY nasal spray is given. If this happens, give another dose every 2 to 3 minutes using a new REZENOPY nasal spray and watch the person closely until emergency help is received.

What is REZENOPY nasal spray?

- REZENOPY nasal spray is a prescription medicine used in adults and children for the treatment of an opioid emergency such as an overdose or a possible opioid overdose with signs of breathing problems and severe sleepiness or not being able to respond.

- REZENOPY nasal spray is to be given right away and does not take the place of emergency medical care. Get emergency medical help right away after giving the first dose of REZENOPY nasal spray, even if the person wakes up.

- REZENOPY nasal spray is safe and effective in children for known or suspected opioid overdose.

Do not use REZENOPY nasal spray if you are allergic to naloxone hydrochloride or any of the ingredients in REZENOPY nasal spray. See the end of this leaflet for a complete list of ingredients in REZENOPY nasal spray.

Before using REZENOPY nasal spray, tell your healthcare provider about all your medical conditions, including if you:

- have heart problems
- are breastfeeding or plan to breastfeed. It is not known if REZENOPY nasal spray passes into your breast milk.

Tell your healthcare provider about the medicines you take, including prescription and over-the-counter medicines, vitamins, and herbal supplements.

How should I use REZENOPY nasal spray?

Read the “Instructions for Use” at the end of this Patient Information leaflet for detailed information about the right way to use REZENOPY nasal spray.

- Use REZENOPY nasal spray exactly as prescribed by your healthcare provider.

- Each REZENOPY nasal spray contains 1 dose of medicine and cannot be reused.
- Lay the person on their back. Support their neck with your hand and allow the head to tilt back before giving REZENOPY nasal spray.
- REZENOPY nasal spray should be given into one nostril.

- If additional doses are needed, give REZENOPY nasal spray in the other nostril.

What are the possible side effects of REZENOPY nasal spray?

REZENOPY nasal spray may cause serious side effects, including:

- Sudden opioid withdrawal symptoms. In someone who has been using opioids regularly, opioid withdrawal symptoms can happen suddenly after receiving REZENOPY nasal spray and may include:

- body aches
- diarrhea
- increased heart rate
- fever
- runny nose
- sneezing
- goose bumps
- sweating
- yawning
- nausea or vomiting
- nervousness
- restlessness or irritability
- shivering or trembling
- stomach cramping
- weakness
- increased blood pressure

In infants under 4 weeks old who have been receiving opioids regularly, sudden opioid withdrawal may be life-threatening if not treated the right way. Signs and symptoms include: seizures, crying more than usual, and increased reflexes.

The most common side effects of REZENOPY nasal spray include: upperstomach-area (abdominal) pain, the common cold, and changes in sense of taste.

These are not all the possible side effects of REZENOPY nasal spray.

Call your doctor for medical advice about side effects. You may report side effects to FDA at 1 800-FDA-1088.

How should I store REZENOPY nasal spray?

- Store REZENOPY nasal spray between 2°C to 25°C (36°F to 77°F).

- Do not freeze. Do not expose to excessive heat above 40°C (104°F).
- Keep REZENOPY nasal spray in its box until ready to use. Protect from light.
- Replace REZENOPY nasal spray before the expiration date on the box.

Keep REZENOPY nasal spray and all medicines out of the reach of children.

General Information about the safe and effective use of REZENOPY nasal spray.

Medicines are sometimes prescribed for purposes other than those listed in a Patient Information leaflet. Do not use REZENOPY nasal spray for a condition for which it was not prescribed. You can ask your pharmacist or healthcare provider for information about REZENOPY nasal spray that is written for health professionals.

What are the ingredients in REZENOPY nasal spray?

Active ingredients: naloxone hydrochloride

Inactive ingredients: glycerin, trisodium citrate dihydrate, hydrochloric acid and sodium hydroxide to adjust pH, and purified water.

REZENOPY nasal spray is not made with natural rubber latex.

Manufactured for: Scienture, LLC, Commack, NY 11725.

For more information, go to www.rezenopy.com or call 1-833-754-4917.

This Patient Information has been approved by the U.S. Food and Drug Administration Issued: 04/2024

INSTRUCTIONS FOR USE

REZENOPY™ (reh zeh' noe pee)

(naloxone HCl) nasal spray

10 mg

You and your family members or caregivers should read the Instructions for Use that comes with REZENOPY nasal spray before using it. Talk to your healthcare provider if you and your family members or caregivers have any questions about the use of REZENOPY nasal spray.

Use REZENOPY nasal spray for known or suspected opioid overdose in adults and children. Use REZENOPY nasal spray exactly as prescribed by your healthcare provider.

Important Information You Need to Know Before Giving REZENOPY nasal spray:

• For use in the nose only.

• Do not remove REZENOPY nasal spray from package until ready to use.

• Each REZENOPY nasal spray device has 1 dose and cannot be reused.

• Do not test or prime REZENOPY nasal spray before use.

REZENOPY nasal spray Parts (Figure A)

Step 1. Check person for signs of suspected opioid overdose

Shout “wake up” and shake the person gently.

Check for the following (Figure B):

- unresponsive
- unconscious or unable to wake up
- slow, shallow, irregular breathing
- fingernails or lips turning blue or purple

Step 2. Position Person

Lay the person flat on their back (Figure C).

Step 3. Remove REZENOPY nasal spray from the box

Peel back from either corner at the top of the package. Then removeREZENOPY nasal spray from package (Figure D).

Step 4. Hold REZENOPY nasal spray

Hold with your index and middle fingers on either side of the nozzle and your thumb on the bottom of the plunger (Figure E).

- Do not apply any pressure until you are ready to give the dose.

Step 5. Prepare to give REZENOPY nasal spray

Provide support behind the neck with your hand and tilt the person’s head back. (Figure F).

Gently insert the nozzle tip all the way into one nostril (Figure G).

Step 6. Give REZENOPY nasal spray

Push the plunger hard and all the way in to give the dose (Figure H).

Remove REZENOPY nasal sprayfrom nostril after dose has been given.

Step 7. Call 911 or get emergency help

Call for emergency help right away (Figure I).

Step 8. Turn person to recovery position and monitor

Put the person into the recovery position by turning them on their side (Figure J).

Watch the person closely for 2 to 3 minutes (Figure J).

Step 9. Give another dose if needed and monitor

If the person does not respond by waking up, to voice or touch, or start breathing normally, another dose may be given.

- Get a new REZENOPY nasal spray from the box.
- Repeat Steps 2 through 6 to give another dose of REZENOPY nasal spray in the other nostril (Figure K).
- If more REZENOPY nasal spray is available, repeat Steps 2 through 6 every 2 to 3 minutes, alternating nostrils, until the person wakes up or medical help arrives.

Stay with the person until medical help arrives.

Return the person to a recovery position (Figure L).

Step 10. Disposing of REZENOPY nasal spray

Throw away (dispose of) the used REZENOPY nasal spray in a place away from children (Figure M).

Storage Information

Storing REZENOPY nasal spray

- Store REZENOPY nasal spray between 2°C to 25°C (36°F to 77°F). Excursions permitted up to 40°C (104°F).
- Do not freeze. Do not expose to excessive heat above 40°C (104°F).
- Keep REZENOPY nasal spray in its box until ready to use. Protect from light.
- Replace REZENOPY nasal spray before the expiration date on the box.

Keep REZENOPY nasal spray and all medicines out of the reach of children.

For more information, go to www.rezenopy.com or call 1-833-754-4917.

This Instructions for Use leaflet has been approved by the U.S. Food and Drug Administration. Issued: 04/2024